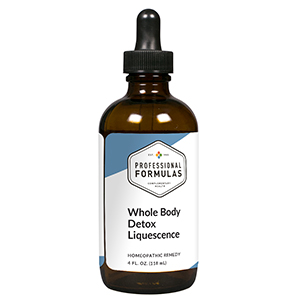 DRUG LABEL: Whole Body Detox Liquescence
NDC: 63083-3035 | Form: LIQUID
Manufacturer: Professional Complementary Health Formulas
Category: homeopathic | Type: HUMAN OTC DRUG LABEL
Date: 20190815

ACTIVE INGREDIENTS: LEMON JUICE 1 [hp_X]/118 mL; TARAXACUM OFFICINALE 2 [hp_X]/118 mL; ARCTOSTAPHYLOS TOMENTOSA WHOLE 2 [hp_X]/118 mL; BERBERIS VULGARIS ROOT BARK 3 [hp_X]/118 mL; CAPSICUM 3 [hp_X]/118 mL; GALIUM APARINE WHOLE 3 [hp_X]/118 mL; LOBELIA INFLATA WHOLE 3 [hp_X]/118 mL; STRYCHNOS NUX-VOMICA SEED 3 [hp_X]/118 mL; SCHISANDRIN B, (+/-)- 3 [hp_X]/118 mL; TYLOPHORA INDICA ROOT 3 [hp_X]/118 mL; SUS SCROFA ADRENAL GLAND 6 [hp_X]/118 mL; BOS TAURUS BRAIN 6 [hp_X]/118 mL; BEEF HEART 6 [hp_X]/118 mL; BOS TAURUS LARGE INTESTINE 6 [hp_X]/118 mL; BEEF KIDNEY 6 [hp_X]/118 mL; BEEF LIVER 6 [hp_X]/118 mL; BEEF LUNG 6 [hp_X]/118 mL; BOS TAURUS LYMPH VESSEL 6 [hp_X]/118 mL; MAGNESIUM PHOSPHATE, DIBASIC TRIHYDRATE 6 [hp_X]/118 mL; BOS TAURUS SPLEEN 6 [hp_X]/118 mL; THYROID, UNSPECIFIED 6 [hp_X]/118 mL; CALCIUM SULFIDE 8 [hp_X]/118 mL; LACTIC ACID, DL- 8 [hp_X]/118 mL
INACTIVE INGREDIENTS: ALCOHOL; WATER

T35

ACTIVE INGREDIENTS

Citrus limonum 1X
Taraxacum officinale 2X
Uva-ursi 2X
Berberis vulgaris 3X
Capsicum annuum 3X
Galium aparine 3X
Lobelia inflata 3X
Nux vomica 3X
Schisandra 3X
Tylophora 3X
Adrenal 6X
Brain 6X
Heart 6X
Intestine 6X
Kidney 6X
Liver 6X
Lung 6X
Lymph 6X
Magnesia phosphorica 6X
Spleen 6X
Thyroid 6X
Hepar sulphuris calcareum 8X
Lacticum acidum 8X

QUESTIONS

Professional Formulas

PO Box 2034 Lake Oswego, OR 97035

INDICATIONS

For the temporary relief of fatigue, lethargy, headaches, muscle or joint pain, mild bloating or gas, disturbed sleep, or lack of concentration.*

PURPOSE

*Claims based on traditional homeopathic practice, not accepted medical evidence. Not FDA evaluated.

WARNINGS

In case of overdose, get medical help or contact a poison control center right away.

Keep out of the reach of children.

PREGNANCY OR BREAST FEEDING

If pregnant or breastfeeding, ask a healthcare professional before use.

DIRECTIONS

Place drops under tongue 30 minutes before/after meals. Adults and children 12 years and over: Take one full dropper up to 2 times per day. Consult a physician for use in children under 12 years of age.

OTHER INFORMATION

Tamper resistant. If seal is broken, do not use. After opening, close container tightly and store at room temperature away from heat.

INACTIVE INGREDIENTS

10% ethanol, 8% vegetable glycerin (from soy), purified water.

LABEL

Est 1985

Professional Formulas

Complementary Health

Whole Body Detox Liquescence

Homeopathic Remedy

4 FL. OZ. (118 mL)